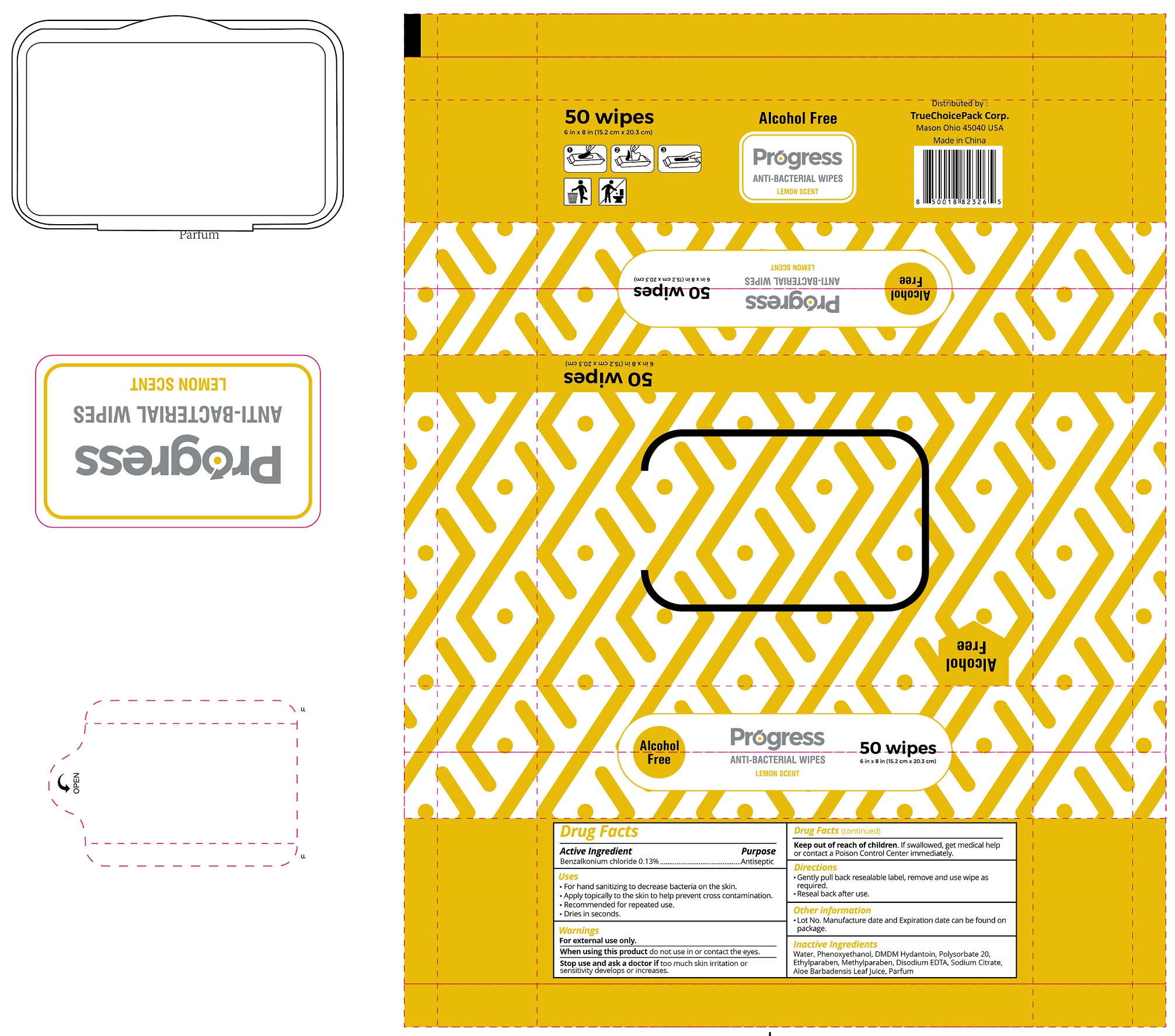 DRUG LABEL: Progress Antibacterial Wipes Lemon Scent
NDC: 80882-002 | Form: CLOTH
Manufacturer: Truechoicepack, Corp
Category: otc | Type: HUMAN OTC DRUG LABEL
Date: 20201125

ACTIVE INGREDIENTS: BENZALKONIUM CHLORIDE 1.3 mg/1 mL
INACTIVE INGREDIENTS: WATER; PHENOXYETHANOL; DMDM HYDANTOIN; POLYSORBATE 20; ETHYLPARABEN; METHYLPARABEN; DISODIUM HYDROGEN CITRATE; ALOE VERA LEAF

Progress Anti-Bacterial Wipes Lemon Scent

Active Ingredient

Benzalkonium chloride 0.13%

Purpose

Antiseptic

Uses

- For hand sanitizing to decrease bacteria on the skin.
- Apply topically to the skin to help prevent cross contamination.
- Recommended for repeated use.
- Dries in seconds.

Warnings

For external use only.

When using this product

do not use in or contact the eyes.

Stop use and ask a doctor is

too much skin irritation or sensitivity develops or increases.

Keep this out of reach of children.

If swallowed, get medical help or contact a Poison Control Center immediately.

Directions

- Gently pull back resealable label, remove and use wipe as required.
- Reseal back after use.

Other information

- Lot No. Manufacture date and Expiration date can be found on package.

Inactive Ingredients

Water, Phenoxyethanol, DMDM Hydantoin, Polysorbate 20, Ethylparaben, Methylparaben, Disodium Citrate, Aloe Barbadensis Leaf Juice, Parfum